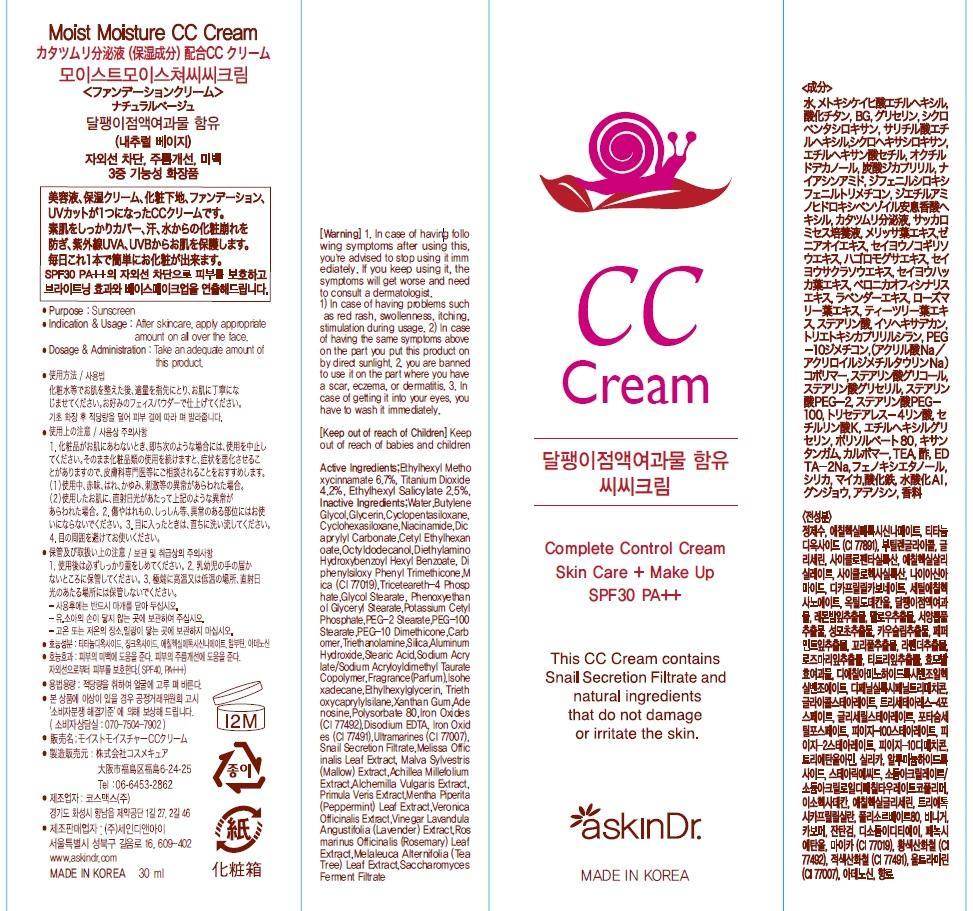 DRUG LABEL: MOIST MOISTURE CC
NDC: 69072-020 | Form: CREAM
Manufacturer: Seindni Co.,ltd
Category: otc | Type: HUMAN OTC DRUG LABEL
Date: 20181210

ACTIVE INGREDIENTS: OCTINOXATE 2.01 mg/30 mL; Titanium Dioxide 1.26 mg/30 mL; OCTISALATE 0.75 mg/30 mL
INACTIVE INGREDIENTS: Water; Butylene Glycol

ACTIVE INGREDIENT

Active Ingredients: Ethylhexyl Methoxycinnamate 6.7%, Titanium Dioxide 4.2%, Ethylhexyl Salicylate 2.5%

INACTIVE INGREDIENT

Inactive Ingredients:
Water,Butylene Glycol,Glycerin,Cyclopentasiloxane, Cyclohexasiloxane,Niacinamide,Dicaprylyl Carbonate,Cetyl Ethylhexanoate,Octyldodecanol,Diethylamino Hydroxybenzoyl Hexyl Benzoate, Diphenylsiloxy Phenyl Trimethicone,Mica (CI 77019),Triceteareth-4 Phosphate,Glycol Stearate, Phenoxyethanol Glyceryl Stearate,Potassium Cetyl
Phosphate,PEG-2 Stearate,PEG-100 Stearate,PEG-10 Dimethicone,Carbomer,Triethanolamine,Silica,Aluminum Hydroxide,Stearic Acid,Sodium Acrylate/Sodium Acryloyldimethyl Taurate Copolymer,Fragrance(Parfum),Isohexadecane,Ethylhexylglycerin, Triethoxycaprylylsilane,Xanthan Gum,Adenosine,Polysorbate 80,Iron Oxides (CI 77492),Disodium EDTA, Iron Oxides (CI 77491),Ultramarines (CI 77007), Snail Secretion Filtrate,Melissa Officinalis Leaf Extract, Malva Sylvestris (Mallow) Extract,Achillea Millefolium Extract,Alchemilla Vulgaris Extract, Primula Veris Extract,Mentha Piperita (Peppermint) Leaf Extract,Veronica Officinalis Extract,Vinegar Lavandula Angustifolia (Lavender) Extract,Rosmarinus Officinalis (Rosemary) Leaf Extract,Melaleuca Alternifolia (Tea Tree) Leaf Extract,Saccharomyces Ferment Filtrate

PURPOSE

Purpose: Sunscreen

WARNINGS

Warning:
1. In case of having following symptoms after using this, you're advised to stop using it immediately. If you keep using it, the symptoms will get worse and need to consult a dermatologist.
1) In case of having problems such as red rash, swollenness, itching, stimulation during usage.
2) In case of having the same symptoms above on the part you put this product on by direct sunlight.
2. you are banned to use it on the part where you have a scar, eczema, or dermatitis.
3. In case of getting it into your eyes, you have to wash it immediately.

Keep out of reach of Children: Keep out of reach of babies and children

INDICATIONS AND USAGE

Indication and Usage: After skincare, apply appropriate amount on all over the face.

Dosage and Administration : Take an adequate amount of this product.